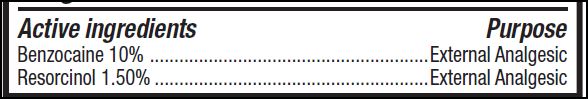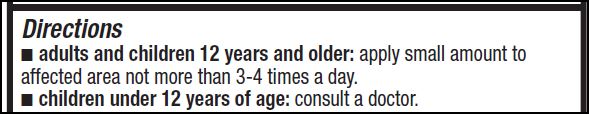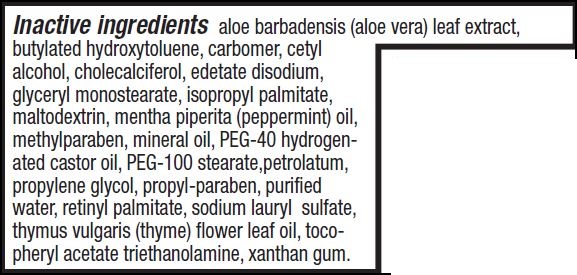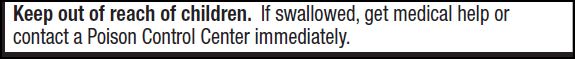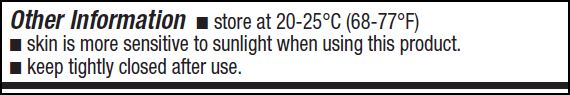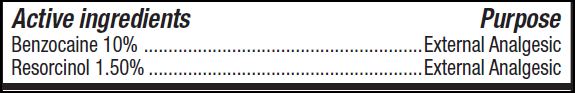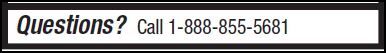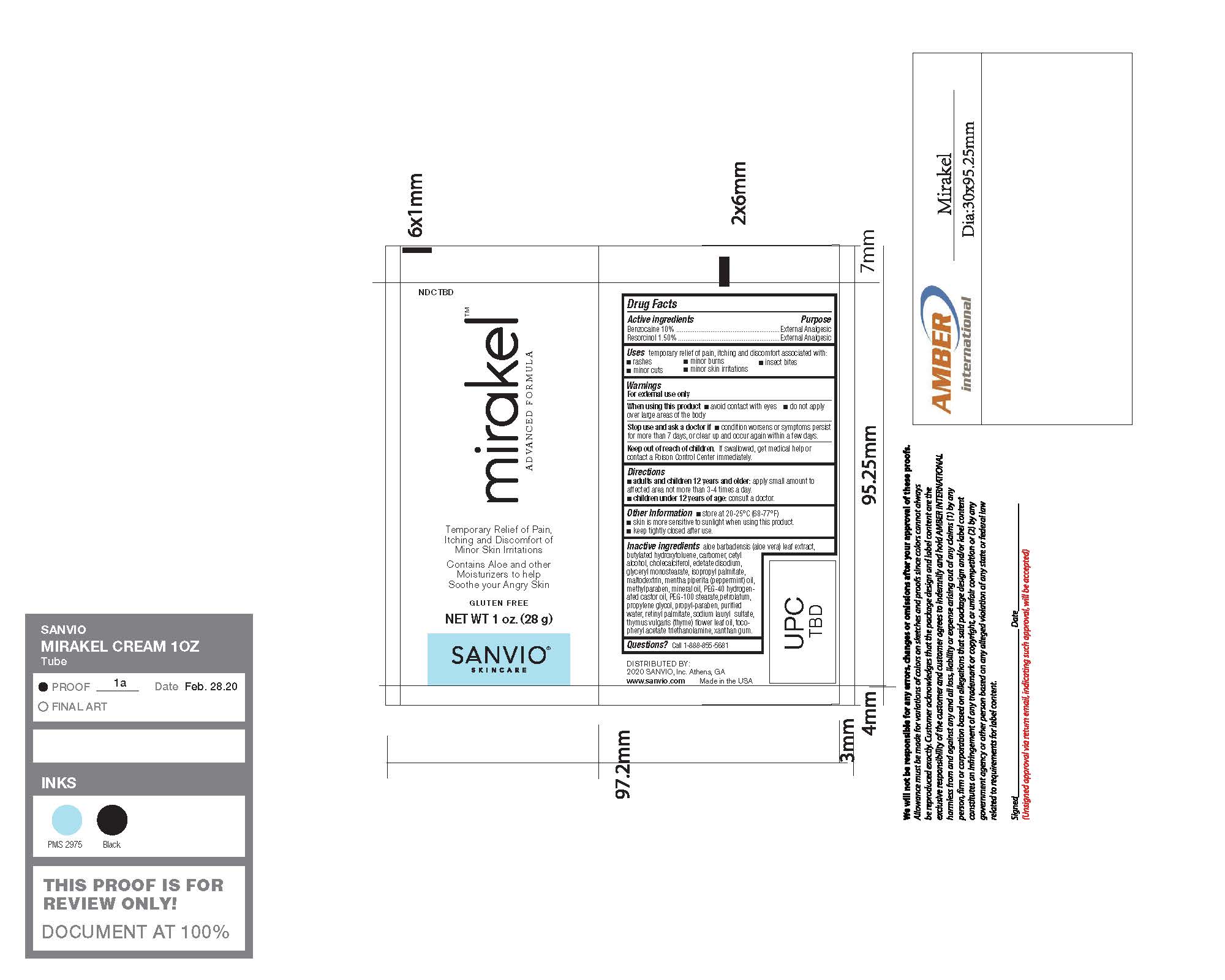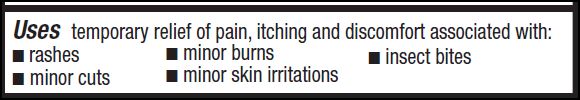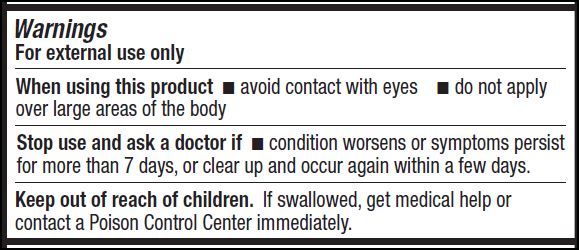 DRUG LABEL: mirakel
NDC: 78589-100 | Form: CREAM
Manufacturer: Sanvio, Inc.
Category: otc | Type: HUMAN OTC DRUG LABEL
Date: 20200715

ACTIVE INGREDIENTS: BENZOCAINE 0.1 g/1 g; RESORCINOL 0.015 g/1 g
INACTIVE INGREDIENTS: CETYL ALCOHOL 0.03 g/1 g

Sanvio Mirakel Cream

Active Ingredients

Active ingredients Purpose
Benzocaine 10% .........................................................External Analgesic
Resorcinol 1.50%........................................................External Analgesic

Uses

Uses temporary relief of pain, itching and discomfort associated with:

■ rashes
■ minor cuts

■ minor burns
■ minor skin irritations

■ insect bites

Warnings

For external use only
When using this product ■ avoid contact with eyes ■ do not apply
over large areas of the body

Stop use and ask a doctor if ■ condition worsens or symptoms persist
for more than 7 days, or clear up and occur again within a few days

Keep out of reach of children. If swallowed, get medical help or
contact a Poison Control Center immediately.

Keep out of reach of children. If swallowed, get medical help or
contact a Poison Control Center immediately.

Directions

■ adults and children 12 years and older: apply small amount to
affected area not more than 3-4 times a day.
■ children under 12 years of age: consult a doctor

Other Information

Other Information ■ store at 20-25°C (68-77°F)
■ skin is more sensitive to sunlight when using this product.
■ keep tightly closed after use.

Inactive Ingredients

Inactive ingredients aloe barbadensis (aloe vera) leaf extract,
butylated hydroxytoluene, carbomer, cetyl
alcohol, cholecalciferol, edetate disodium,
glyceryl monostearate, isopropyl palmitate,
maltodextrin, mentha piperita (peppermint) oil,
methylparaben, mineral oil, PEG-40 hydrogenated
castor oil, PEG-100 stearate,petrolatum,
propylene glycol, propyl-paraben, purified
water, retinyl palmitate, sodium lauryl sulfate,
thymus vulgaris (thyme) flower leaf oil, tocopheryl
acetate triethanolamine, xanthan gum.

Questions

Questions? Call 1-888-855-5681

Purpose

Active ingredients Purpose
Benzocaine 10% .........................................................External Analgesic
Resorcinol 1.50%........................................................External Analgesic